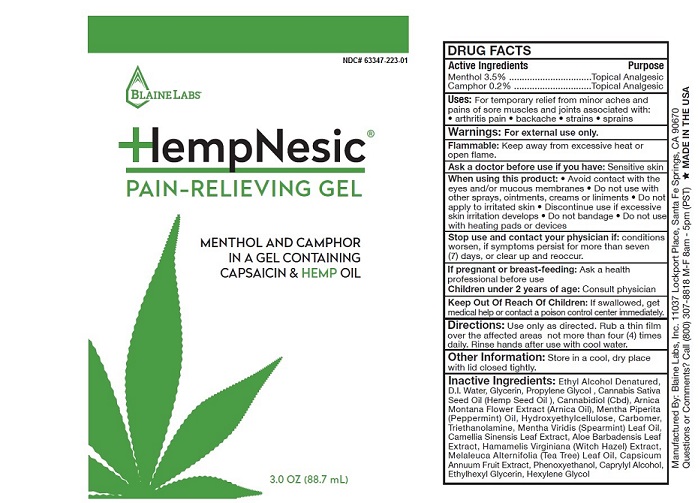 DRUG LABEL: HempNesic
NDC: 63347-223 | Form: GEL
Manufacturer: Blaine Labs Inc.
Category: otc | Type: HUMAN OTC DRUG LABEL
Date: 20231221

ACTIVE INGREDIENTS: MENTHOL 3.5 g/100 mL; CAMPHOR (SYNTHETIC) .2 g/100 mL
INACTIVE INGREDIENTS: ALCOHOL; Water; GLYCERIN; PROPYLENE GLYCOL; CANNABIS SATIVA SEED OIL; CANNABIDIOL; ARNICA MONTANA FLOWER; PEPPERMINT OIL; CETYL HYDROXYETHYLCELLULOSE (350000 MW); CARBOMER 1342; TROLAMINE; SPEARMINT OIL; GREEN TEA LEAF; ALOE VERA LEAF; HAMAMELIS VIRGINIANA TOP; TEA TREE OIL; PAPRIKA; PHENOXYETHANOL; CAPRYLIC ALCOHOL; ETHYLHEXYLGLYCERIN; HEXYLENE GLYCOL

HempNesic®
PAIN-RELIEVING GEL

DRUG FACTS Active Ingredients:

Menthol 3.5%

Camphor 0.2%

Purpose

Topical Analgesic

Uses

For temporary relief from minor aches and
pains of sore muscles and joints asociated with:
• arthritis pain • backache • strains • sprains

Warnings:

For external use only.

Flammable:

Keep away from excessive heat or open flame.

Ask a doctor before use if you have:

Sensitive skin

When using this product:

• Avoid contact with the eyes and/or mucous membranes • Do not use with
other sprays, ointments, creams or liniments • Do not apply to irritated skin, & discontinue use if excessive
skin irritation develops • Do not bandage • Do not use with heating pads or device

Stop use and contact your physician if:

conditions worsen, or if symptoms persist for more than seven (7)
days, or clear up and reoccur.

If pregnant or breast-feeding:

Ask a health professional before use

Children under 2 years of age:

Consult physician

Keep Out Of Reach Of Children:

If swallowed, get medical help or contact a poison control center immediately.

Directions:

Use only as directed. Rub a thin film over the affected areas not more than four (4) times
daily. Rinse hands after use with cool water.

Other Information:

Store in a cool, dry place with lid closed tightly.

Inactive Ingredients

Ethyl Alcohol Denatured, D.I. Water, Glycerin, Propylene Glycol,
Cannabis Sativa Seed Oil (Hemp Seed Oil), Cannabidiol (CBD), Arnica Montana Flower
Extract (Arnica Oil), Mentha Piperita (Peppermint) Oil, Hydroxyethylcellulose, Carbomer,
triethanolamine, Mentha Viridis (Spearmint) Leaf Oil, Camellia Sinensis Leaf
Extract, Aloe Barbadensis Leaf Extract, Hamamelis Virginiana (Witch Hazel)
Extract, Melaleuca Alternifolia (Tea Tree) Leaf Oil, Capsicum Annuum Fruit
Extract, Phenoxyethanol, Caprylyl Alcohol, Ethylhexyl Glycerin, Hexylene Glycol

HempNesic® PAIN-RELIEVING GEL

NDC 63347-223-01

BLAINE LABS®

HempNesic ®
PAIN-RELIEVING GEL

MENTHOL AND CAMPHOR
IN A GEL CONTAINING
CAPSAICIN & HEMP OIL

3.0 OZ (88.7 mL)

DRUG FACTS

Active Ingredients Purpose
Menthol 3.5% ................................Topical Analgesic
Camphor 0.2% ..............................Topical Analgesic

Uses: For temporary relief from minor aches and
pains of sore muscles and joints asociated with:
• arthritis pain • backache • strains • sprains

Warnings: For external use only.

Flammable: Keep away from excessive heat or open flame.

Ask a doctor before use if you have: Sensitive skin

When using this product: • Avoid contact with the
eyes and/or mucous membranes • Do not use with
other sprays, ointments, creams or liniments • Do not
apply to irritated skin, & discontinue use if excessive
skin irritation develops • Do not bandage • Do not use
with heating pads or device

Stop use and contact your physician if: conditions
worsen, or if symptoms persist for more than seven (7)
days, or clear up and reoccur.

If pregnant or breast-feeding: Ask a health
professional before use

Children under 2 years of age: Consult physician

Keep Out Of Reach Of Children: If swallowed, get
medical help or contact a poison control center immediately.

Directions: Use only as directed. Rub a thin film
over the affected areas not more than four (4) times
daily. Rinse hands after use with cool water.

Other Information: Store in a cool, dry place with lid closed tightly.

Inactive Ingredients: Ethyl Alcohol Denatured, D.I. Water,
Glycerin, Propylene Glycol, Cannabis Sativa Seed Oil (Hemp Seed Oil),
Cannabidiol (Cbd), Arnica Montana Flower Extract (Arnica Oil),
Mentha Piperita (Peppermint) Oil, Hydroxyethylcellulose, Carbomer,
Triethanolamine, Mentha Viridis (Spearmint) Leaf Oil, Camellia
Sinensis Leaf Extract, Aloe Barbadensis Leaf Extract,
Hamamelis Virginiana (Witch Hazel) Extract, Melaleuca Alternifolia (Tea Tree)
Leaf Oil, Capsicum Annuum Fruit Extract, Phenoxyethanol,
Caprylyl Alcohol, Ethylhexyl Glycerin, Hexylene Glycol

Manufactured By: Blaine Labs, Inc. 11037 Lockport Place, Santa Fe Springs, CA 90670

Questions or Comments? Call (800) 307-8818 M-F 8am - 5pm (PST) *MADE IN THE USA

Hempnesic_223_01.jpg